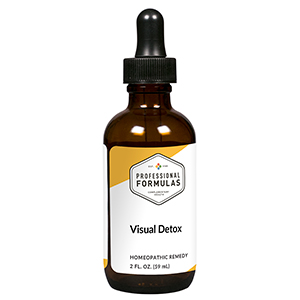 DRUG LABEL: Visual Detox
NDC: 63083-6037 | Form: LIQUID
Manufacturer: Professional Complementary Health Formulas
Category: homeopathic | Type: HUMAN OTC DRUG LABEL
Date: 20190815

ACTIVE INGREDIENTS: TAURINE 6 [hp_X]/59 mL; ZEAXANTHIN 6 [hp_X]/59 mL; BOS TAURUS EYE 6 [hp_X]/59 mL; GLUTATHIONE 8 [hp_X]/59 mL; GERMANIUM 9 [hp_X]/59 mL; GRAPHITE 12 [hp_X]/59 mL; SEPIA OFFICINALIS JUICE 12 [hp_X]/59 mL; BILBERRY 12 [hp_X]/59 mL; HUMAN ADENOVIRUS B SEROTYPE 3 30 [hp_X]/59 mL; CARBON DISULFIDE 30 [hp_X]/59 mL; CHLAMYDIA TRACHOMATIS 30 [hp_X]/59 mL; CHLOROQUINE 30 [hp_X]/59 mL; HUMAN HERPESVIRUS 1 30 [hp_X]/59 mL; INFLUENZA A VIRUS A/VICTORIA/2454/2019 IVR-207 (H1N1) ANTIGEN (FORMALDEHYDE INACTIVATED) 30 [hp_X]/59 mL; GONORRHEAL URETHRAL SECRETION HUMAN 30 [hp_X]/59 mL; NAJA NAJA VENOM 30 [hp_X]/59 mL; NAPHTHALENE 30 [hp_X]/59 mL; STAPHYLOCOCCUS AUREUS 30 [hp_X]/59 mL
INACTIVE INGREDIENTS: ALCOHOL; WATER

X37

ACTIVE INGREDIENTS

Taurine 6X
Lutein/Zeaxanthin 6X, 8X
Eye 6X, 30X, 100X
Glutathione 8X
Germanium 9X, 12X, 30X
Graphites 12X
Sepia 12X
Vaccinium myrtillus 12X
Adenovirus 30X
Carboneum sulphuratum 30X
Chlamydia pneumoniae 30X
Chlamydia trachomatis 30X
Chloroquine 30X
Herpes simplex/zoster 30X
Influenzinum 30X
Medorrhinum 30X
Naja tripudians 30X
Naphthalinum 30X
Staphylococcus 30X

QUESTIONS

Professional Formulas

PO Box 2034 Lake Oswego, OR 97035

INDICATIONS

Temporarily relieves occasional blurred or distorted vision, seeing floaters or spots, sensitivity to light, or red, painful eyes or eyelids*

PURPOSE

*Claims based on traditional homeopathic practice, not accepted medical evidence. Not FDA evaluated.

WARNINGS

Consult a doctor if condition worsens or symptoms persist. Keep out of the reach of children. In case of overdose, get medical help or contact a poison control center right away. If pregnant or breastfeeding, ask a healthcare professional before use.

Keep out of the reach of children.

PREGNANCY OR BREAST FEEDING

If pregnant or breastfeeding, ask a healthcare professional before use.

DIRECTIONS

Place drops under tongue 30 minutes before/after meals. Adults and children 12 years and over: Take 10 drops up to 3 times per day. Consult a physician for use in children under 12 years of age.

OTHER INFORMATION

Tamper resistant. If seal is broken, do not use. After opening, close container tightly and store at room temperature away from heat.

INACTIVE INGREDIENTS

20% ethanol, purified water.

LABEL

Est 1985

Professional Formulas

Complementary Health

Visual Detox

Homeopathic Remedy

2 FL. OZ. (59 mL)